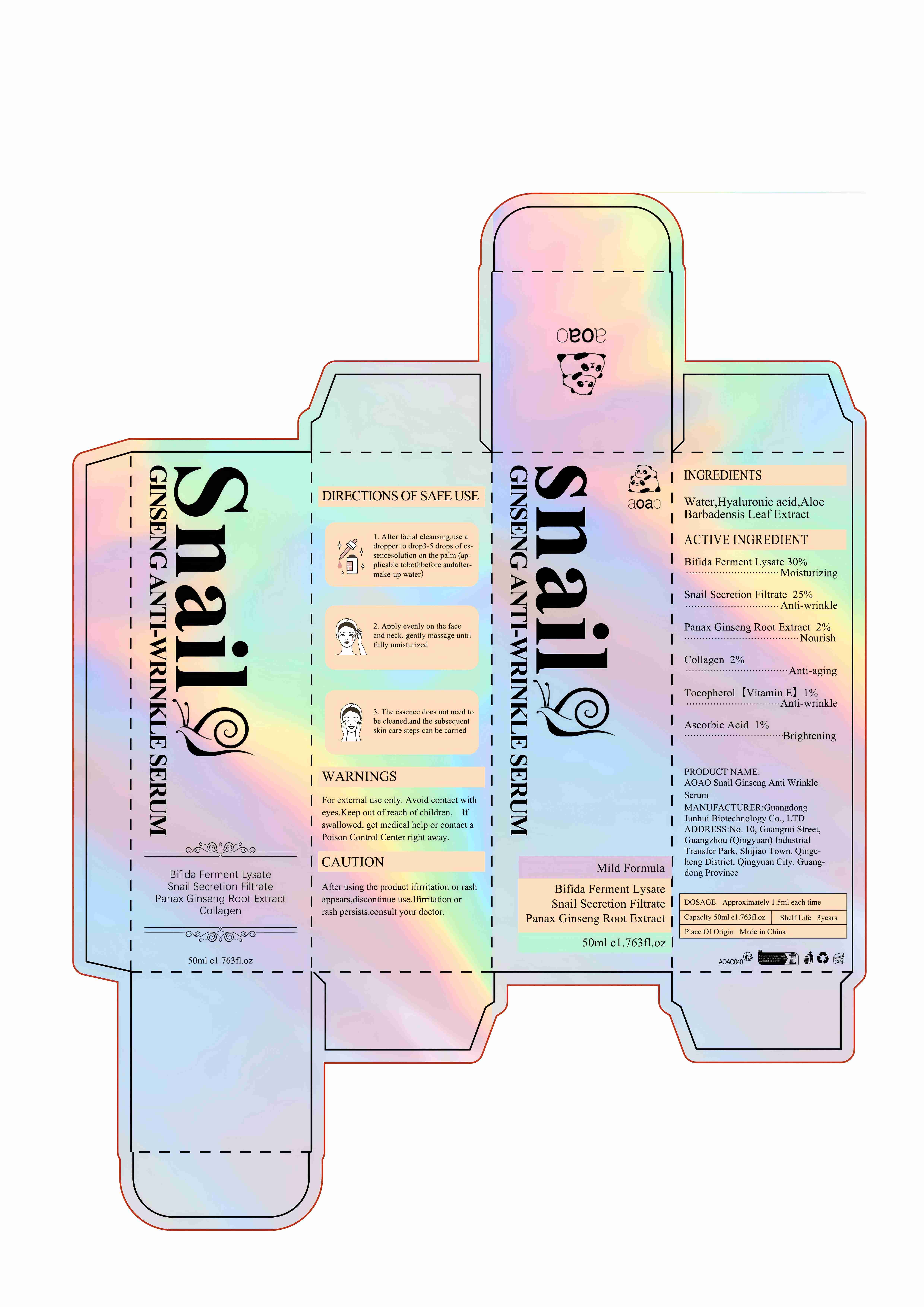 DRUG LABEL: AOAO Snail Ginseng Anti Wrinkle Serum
NDC: 84509-018 | Form: LIQUID
Manufacturer: Guangdong Junhui Biotechnology Co., LTD
Category: otc | Type: HUMAN OTC DRUG LABEL
Date: 20240923

ACTIVE INGREDIENTS: COLLAGEN, SOLUBLE, FISH SKIN 1000 mg/50 mL; TOCOPHEROL 500 mg/50 mL; GARDEN SNAIL MUCIN 12500 mg/50 mL; ASCORBIC ACID 500 mg/50 mL; FERMENT COMPLEX 6/PF 15000 mg/50 mL; ASIAN GINSENG 1000 mg/50 mL
INACTIVE INGREDIENTS: WATER; ALOE VERA LEAF; HYALURONIC ACID

Active Ingredients

Bifida Ferment Lysate 30%
Snail Secretion Filtrate 25%
Panax Ginseng Root Extract 2%
Collagen 2%
Tocopherol 1%
Ascorbic Acid 1%

Purpose

Moisturizing
Anti-wrinkle
Nourish
Anti-aging
Anti-fading
Brightening

Uses

1. After facial cleansing,use a dropper to drop3-5 drops of essencesolution on the palm (applicable tobothbefore andaftermake-up water）
2. Apply evenly on the face and neck, gently massage until fully moisturized
3. The essence does not need to be cleaned,and the subsequent skin care steps can be carried out after it is fully absorbed

Warnings

For external use only. Keep out ofreach of children.Avoid contact with eyes

Keep out of reach of children

If swallowed, get medical help or contact a Poison Control Center right away

CAUTION

After using the product ifirritation or rash appears,discontinue use.Ifirritation or
rash persists.consult your doctor.

DOSAGE

Approximately 1.5ml each time

Product Name

AOAO Snail Ginseng Anti Wrinkle Serum

Inactive Ingredients

Water,Hyaluronic acid,Aloe Barbadensis Leaf Extract.

Manufacturer

Guangdong Junhui Biotechnology Co., LTD

ADDRESS

No. 10, Guangrui Street, Guangzhou (Qingyuan) Industrial Transfer Park, Shijiao Town, Qingcheng District, Qingyuan City, Guangdong Province

Capacity

50ml e1.763f1.oz

Shelf Life

3 Years

Place of Origin

Made in China